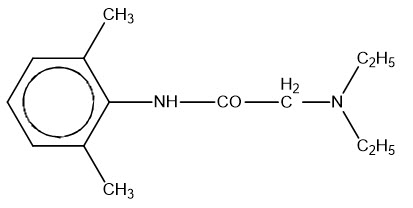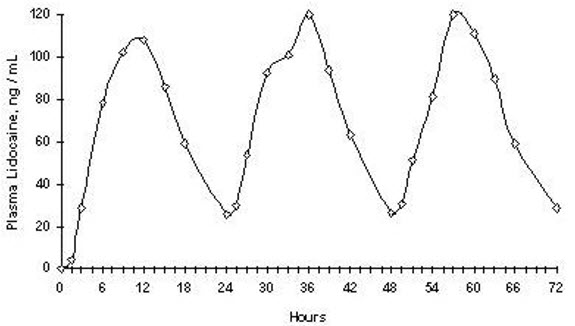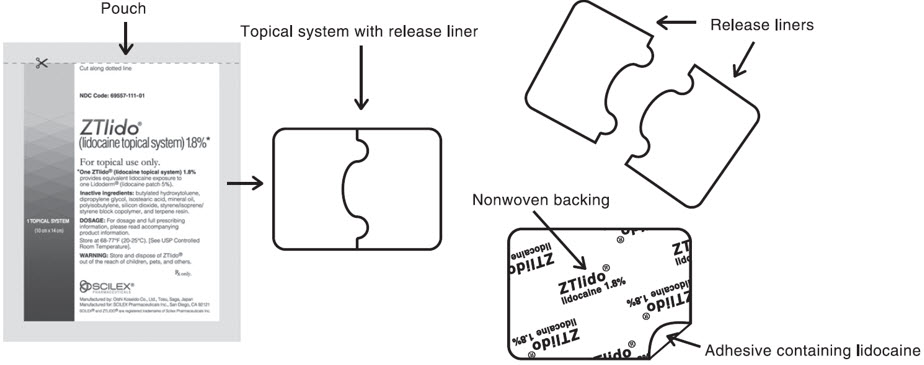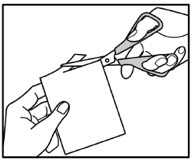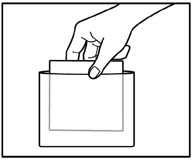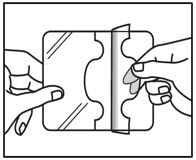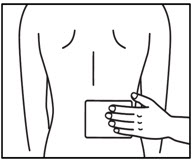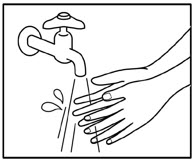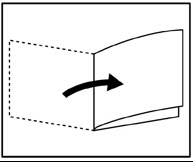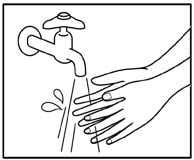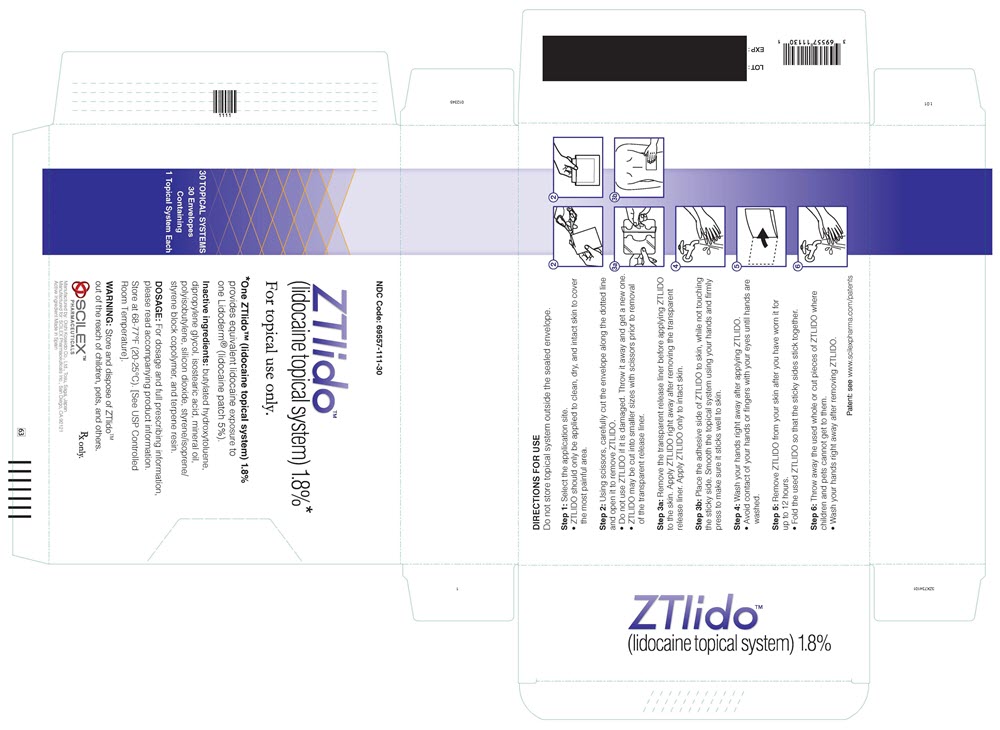 DRUG LABEL: Ztlido
NDC: 69557-111 | Form: PATCH
Manufacturer: Scilex Pharmaceuticals Inc.
Category: prescription | Type: HUMAN PRESCRIPTION DRUG LABEL
Date: 20241101

ACTIVE INGREDIENTS: LIDOCAINE 36 mg/1 1
INACTIVE INGREDIENTS: DIPROPYLENE GLYCOL; MINERAL OIL; ISOSTEARIC ACID; POLYISOBUTYLENE (1100000 MW); BUTYLATED HYDROXYTOLUENE; POLYISOBUTYLENE (55000 MW); SILICON DIOXIDE

HIGHLIGHTS OF PRESCRIBING INFORMATION

These highlights do not include all the information needed to use ZTLIDO®safely and effectively. See full prescribing information for ZTLIDO®.
ZTLIDO®(lidocaine topical system)
Initial U.S. Approval: 1953

RECENT MAJOR CHANGES

Dosage and Administration (2.1) | 4/2021

1 INDICATIONS AND USAGE

ZTLIDO contains lidocaine, an amide local anesthetic, and is indicated for relief of pain associated with post-herpetic neuralgia (PHN) in adults (1).

2 DOSAGE AND ADMINISTRATION

- Because of the difference in bioavailability of ZTLIDO compared to Lidoderm®, a different dosage strength is required to be administered to the patient. One ZTLIDO (lidocaine topical system) 1.8% provides equivalent lidocaine exposure to one Lidoderm (lidocaine patch 5%). (2.1)
- Apply ZTLIDO to intact skin to cover the most painful area. Apply the prescribed number of topical systems (maximum of 3) only once for up to 12 hours in a 24-hour period. (2.2)
- ZTLIDO may be cut into smaller sizes prior to removal of the release liner. (2.2)
- In patients who are debilitated or have impaired elimination, smaller areas of treatment are recommended. Achieve this by cutting ZTLIDO with scissors into a smaller size prior to removing the release liner. (2.2)

3 DOSAGE FORMS AND STRENGTHS

ZTLIDO 1.8% is available as a single-dose topical system. (3)

4 CONTRAINDICATIONS

ZTLIDO is contraindicated in patients with a known history of sensitivity to local anesthetics of the amide type, or to any other component of the product. (4)

5 WARNINGS AND PRECAUTIONS

- Accidental Exposure: Even a used ZTLIDO topical system contains residual lidocaine after use. It is important for patients to store and dispose of ZTLIDO properly and keep out of the reach of children, pets, and others. (5.1)
- Excessive Dosing/Overexposure: Applying ZTLIDO to larger surface areas or for a longer duration than recommended could lead to increased absorption and high blood concentrations of lidocaine, leading to adverse effects. (5.2)
- Increased Absorption on Non-Intact Skin: May result in higher blood concentrations of lidocaine. (5.2)
- Risk of Overexposure with External Heat Sources: Applying external heat sources to ZTLIDO may result in increased drug exposure. (5.2)
- Methemoglobinemia: Cases of methemoglobinemia have been reported in association with local anesthetic use. (5.3)
- Application Site Reactions: During or immediately after treatment with ZTLIDO, application site reactions may develop. (5.4)
- Hypersensitivity Reactions: Cross sensitivity to ZTLIDO in patients with a history of drug sensitivity to para-aminobenzoic acid (PABA) derivatives is possible. (5.5)
- Eye Exposure: Immediately wash out the eye with water or saline and protect the eye until sensation returns. (5.6).

6 ADVERSE REACTIONS

Common adverse reactions are application site reactions such as irritation, erythema, and pruritus. (6)

To report SUSPECTED ADVERSE REACTIONS, contact Scilex Pharmaceuticals Inc. at 1-866-SCILEX3 or FDA at 1-800-FDA-1088 or www.fda.gov/medwatch.

7 DRUG INTERACTIONS

- Class I Antiarrhythmic Drugs:When ZTLIDO is used in patients receiving Class I antiarrhythmic drugs (such as tocainide and mexiletine) the toxic effects are additive and potentially synergistic. Consider risk/benefit before concomitant use. (7.2)
- Local Anesthetic Agents:When ZTLIDO is used concomitantly with other products containing local anesthetic agents, the effects are additive. Consider the amount of drug absorbed from all formulations when local anesthetics are administered concomitantly. (7.3)

8 USE IN SPECIFIC POPULATIONS

Lactation: Lidocaine is excreted into human milk. Caution should be exercised when ZTLIDO is administered to a nursing mother, especially when administered with other local anesthetics. (8.2)

FULL PRESCRIBING INFORMATION

1 INDICATIONS AND USAGE

ZTLIDO is indicated for relief of pain associated with post-herpetic neuralgia (PHN) in adults.

2 DOSAGE AND ADMINISTRATION

2.1 Important Dosage and Administration Instructions

Because of the difference in bioavailability of ZTLIDO compared to Lidoderm (lidocaine patch 5%), a different dosage strength is required to be administered to the patient. One ZTLIDO (lidocaine topical system) 1.8% provides equivalent lidocaine exposure to one Lidoderm (lidocaine patch 5%) [see Clinical Pharmacology (12.3)].

When ZTLIDO is used concomitantly with other products containing local anesthetic agents, the total amount of drug absorbed from all formulations must be considered.

Clearly instruct and advise patients:

- to wash hands immediately after handling ZTLIDO and to avoid contact with eyes [see Warnings and Precautions (5.6)] .
- to store ZTLIDO inside the sealed envelope out of the reach of children, pets, and others and to apply immediately after removal from the envelope.
- to fold used ZTLIDO so that the adhesive side sticks to itself and to safely discard used ZTLIDO or pieces of cut ZTLIDO where children and pets cannot get to them [see Warnings and Precautions (5.1)] .
- to never apply external heat sources, such as heating pads or electric blankets, directly to ZTLIDO, because plasma lidocaine levels are increased. ZTLIDO can be applied, however, to the administration site after moderate heat exposure, such as 15 minutes of heating pad exposure on a medium setting [see Warnings and Precautions (5.2), Clinical Pharmacology (12.3)] .
- that clothing may be worn over the area of application.
- that ZTLIDO may be used during moderate exercise, such as biking for 30 minutes.
- that ZTLIDO may be exposed to water, such as showering for 10 minutes or immersion for 15 minutes.
- to dry the topical system, after water exposure, by gently patting the skin, not by rubbing the skin or topical system.
- that ZTLIDO topical systems that have lifted at the edges may be reattached by pressing firmly on the edges and that fully detached topical systems may be reapplied as originally directed.
- that if a ZTLIDO topical system comes off completely and will not stick to patient's skin, to remove and properly dispose of the used ZTLIDO and to apply a new ZTLIDO topical system for a total duration of 12 hours of used and new topical system together.
- that if irritation or a burning sensation occurs during application, to remove ZTLIDO and to not reapply until the irritation subsides [see Warnings and Precautions (5.4)] .

2.2 Treatment of Post-Herpetic Neuralgia

Advise patients to apply ZTLIDO to intact skin to cover the most painful area and to apply the prescribed number of topical systems (maximum of 3), only once for up to 12 hours within a 24-hour period (12 hours on and 12 hours off) [see Warnings and Precautions (5.2)] .

In patients who are debilitated or have impaired elimination, smaller areas of treatment are recommended. Achieve this by cutting ZTLIDO with scissors into a smaller size prior to removing the release liner.

3 DOSAGE FORMS AND STRENGTHS

Topical system: 1.8% packaged in an individual envelope.

4 CONTRAINDICATIONS

ZTLIDO is contraindicated in patients with a known history of sensitivity to local anesthetics of the amide type, or to any other component of the product.

5 WARNINGS AND PRECAUTIONS

5.1 Accidental Exposure

A used ZTLIDO topical system contains residual lidocaine after use. The potential exists for a small child or a pet to suffer serious adverse effects from chewing or ingesting a new or used ZTLIDO. It is important for patients to store and dispose of ZTLIDO properly, and keep out of the reach of children, pets, and others [see Dosage and Administration (2.1)].

5.2 Excessive Dosing/Overexposure to Lidocaine

Lidocaine toxicity can be expected at lidocaine blood concentrations above 5 mcg/mL. The blood concentration of lidocaine is determined by the rate and extent of lidocaine absorption and elimination. Longer duration of application, application of more than the recommended number of ZTLIDO, smaller patients, or impaired elimination may all contribute to increasing the blood concentration of lidocaine.

If lidocaine overdose is suspected, check drug blood concentration. Management of overdose includes close monitoring, supportive care, and symptomatic treatment [see Overdosage (10)] .

Improper Application and Duration of Use: Application of more than the recommended number of ZTLIDO or applying ZTLIDO for longer than the recommended wearing time (12 hours of every 24 hours) could result in increased absorption and high blood concentrations of lidocaine, leading to adverse reactions. Advise patients on proper application and duration.

Hepatic Disease: Impaired elimination may contribute to increasing blood concentrations of lidocaine. Patients with severe hepatic disease are at greater risk of developing toxic blood concentrations of lidocaine because of their inability to metabolize lidocaine normally.

Use on Non-Intact Skin: Application to broken or inflamed skin, although not tested, may result in higher blood concentrations of lidocaine from increased absorption. ZTLIDO is only recommended for use on intact skin. Advise patients not to apply ZTLIDO to non-intact skin.

External Heat Sources: External heat sources may increase drug exposure, leading to overexposure to lidocaine. Advise patients not to apply external heat sources to ZTLIDO during administration [see Clinical Pharmacology (12.3)].

5.3 Methemoglobinemia

Cases of methemoglobinemia have been reported in association with local anesthetic use. Although all patients are at risk for methemoglobinemia, patients with glucose-6-phosphate dehydrogenase deficiency, congenital or idiopathic methemoglobinemia, cardiac or pulmonary compromise, infants under 6 months of age, and concurrent exposure to oxidizing agents or their metabolites are more susceptible to developing clinical manifestations of the condition. If local anesthetics must be used in these patients, close monitoring for symptoms and signs of methemoglobinemia is recommended.

Signs of methemoglobinemia may occur immediately or may be delayed some hours after exposure, and are characterized by a cyanotic skin discoloration and/or abnormal coloration of the blood. Methemoglobin levels may continue to rise; therefore, immediate treatment is required to avert more serious central nervous system and cardiovascular adverse effects, including seizures, coma, arrhythmias, and death. Discontinue ZTLIDO and any other oxidizing agents. Depending on the severity of the signs and symptoms, patients may respond to supportive care, i.e., oxygen therapy, hydration. A more severe clinical presentation may require treatment with methylene blue, exchange transfusion, or hyperbaric oxygen.

5.4 Application Site Reactions

During or immediately after treatment with ZTLIDO, the skin at the site of application may develop blisters, bruising, burning sensation, depigmentation, dermatitis, discoloration, edema, erythema, exfoliation, irritation, papules, petechia, pruritus, vesicles, or may be the locus of abnormal sensation. These reactions are generally mild and transient, resolving spontaneously within a few minutes to hours. If application site reactions occur while the topical system is being worn, advise the patient to remove ZTLIDO and not to reapply until skin reactions subside.

5.5 Hypersensitivity Reactions

Patients allergic to para-aminobenzoic acid (PABA) derivatives (procaine, tetracaine, benzocaine, etc.) have not shown cross-sensitivity to lidocaine. However, be aware of the potential for cross-sensitivity in patients allergic to PABA derivatives, especially if the etiologic agent is uncertain. Manage hypersensitivity reactions by conventional means. The detection of sensitivity by skin testing is of doubtful value.

5.6 Eye Exposure

The contact of ZTLIDO with eyes, although not studied, should be avoided based on findings of severe eye irritation with the application of similar products in animals. If eye contact occurs, immediately wash out the eye with water or saline and protect the eye (such as, eye glasses/eye wear) until sensation returns.

6 ADVERSE REACTIONS

The following serious adverse reactions are described elsewhere in the labeling:

- Excessive Dosing/Overexposure to Lidocaine [see Warnings and Precautions (5.2)]
- Methemoglobinemia [see Warnings and Precautions (5.3)]
- Application Site Reactions [see Warnings and Precautions (5.4)]
- Hypersensitivity Reactions [see Warnings and Precautions (5.5)]
- Eye Irritation [see Warnings and Precautions (5.6)]

The following adverse reactions from voluntary reports or clinical studies have been reported with lidocaine. Because some of these reactions were reported voluntarily from a population of uncertain size, it is not always possible to reliably estimate their frequency or establish a causal relationship to drug exposure.

Skin and subcutaneous tissues: blisters, bruising, burning sensation, depigmentation, dermatitis, discoloration, edema, erosions, erythema, exfoliation, flushing, irritation, papules, petechia, pruritus, vesicles, and abnormal sensation.

Immune system: angioedema, bronchospasm, dermatitis, dyspnea, hypersensitivity, laryngospasm, pruritus, shock, and urticaria.

Central Nervous System: lightheadedness, nervousness, apprehension, euphoria, confusion, dizziness, drowsiness, tinnitus, blurred or double vision, sensations of heat, cold or numbness, twitching, tremors, convulsions, unconsciousness, somnolence, respiratory depression and arrest.

Cardiovascular: bradycardia, hypotension, and cardiovascular collapse leading to arrest.

Other: asthenia, disorientation, headache, hyperesthesia, hypoesthesia, metallic taste, nausea, pain exacerbated, paresthesia, taste alteration, and vomiting.

7 DRUG INTERACTIONS

7.1 Drugs That May Cause Methemoglobinemia When Used with ZTLIDO

Patients who are administered local anesthetics may be at increased risk of developing methemoglobinemia when concurrently exposed to the following drugs, which could include other local anesthetics:

Examples of Drugs Associated with Methemoglobinemia:

Class | Examples
Nitrates/Nitrites | nitric oxide, nitroglycerin, nitroprusside, nitrous oxide
Local anesthetics | articaine, benzocaine, bupivacaine, lidocaine, mepivacaine, prilocaine, procaine, ropivacaine, tetracaine
Antineoplastic agents | cyclophosphamide, flutamide, hydroxyurea, ifosfamide, rasburicase
Antibiotics | dapsone, nitrofurantoin, para-aminosalicyclic acid, sulfonamides
Antimalarials | chloroquine, primaquine
Anticonvulsants | phenobarbital, phenytoin, sodium valproate
Other drugs | acetaminophen, metoclopramide, quinine, sulfasalazine

7.2 Antiarrhythmic Drugs

When ZTLIDO is used in patients receiving Class I antiarrhythmic drugs (such as tocainide and mexiletine), the toxic effects are additive and potentially synergistic. Consider risk/benefit during concomitant use.

7.3 Local Anesthetics

When ZTLIDO is used concomitantly with other products containing local anesthetic agents, the effects are additive. Consider the amount of drug absorbed from all formulations when local anesthetic agents are administered concomitantly.

8 USE IN SPECIFIC POPULATIONS

8.1 Pregnancy

Risk Summary

The limited human data with lidocaine in pregnant woman are not sufficient to inform drug-associated risk for major birth defects and miscarriage.

The use of lidocaine for labor neuraxial analgesia has not been associated with an increased incidence of adverse fetal effects either during delivery or during the neonatal period (see Data) . Should ZTLIDO be used concomitantly with other products containing lidocaine, consider total drug doses contributed by all formulations.

In a published animal reproduction study, pregnant rats administered lidocaine by continuous subcutaneous infusion at a dose approximately 45 times the maximum recommended daily dose (MRDD) of 108 mg in ZTLIDO during the period of organogenesis resulted in lower fetal body weights. In a published animal reproduction study, pregnant rats administered lidocaine, containing 1:100,000 epinephrine, injected into the masseter muscle of the jaw or into the gum of the lower jaw at 0.5 times the MRDD on Gestation Day 11 resulted in developmental delays in neonates (see Data) .

The estimated background risk of major birth defects and miscarriage for the indicated population is unknown. All pregnancies carry some risk of birth defects, loss, or other adverse outcomes. In the U.S. general population, the estimated background risk of major birth defects and miscarriage in clinically recognized pregnancies is 2% to 4% and 15% to 20%, respectively.

Data

Human Data

In 22 parturient women given 1.5% lidocaine epidural anesthesia, there were no effects on neonatal behavior, using the early neonatal neurobehavioral scale (ENNS). Neuraxial analgesia also did not affect fetal heart rate, beat-to-beat variability, or uterine activity.

Animal Data

Reproductive studies with lidocaine have been performed in rats at doses up to 30 mg/kg (2.7 times the maximum recommended daily dose [MRDD] of 108 mg from ZTLIDO on a mg/m^2basis) subcutaneously and have revealed no evidence of harm to the fetus due to lidocaine.

In a published study, lidocaine administered to pregnant rats by continuous subcutaneous infusion during the period of organogenesis at 100, 250, and 500 mg/kg/day, did not produce any structural abnormalities, but did result in lower fetal weights at 500 mg/kg/day dose (approximately 45 times the MRDD on a mg/m^2basis) in the absence of maternal toxicity.

In a published study, lidocaine containing 1:100,000 epinephrine at a dose of 6 mg/kg (approximately 0.5 times the MRDD on a mg/m^2basis) injected into the masseter muscle of the jaw or into the gum of the lower jaw of pregnant Long-Evans hooded rats on Gestation Day 11 resulted in developmental delays in the neonates. Developmental delays were observed for negative geotaxis, static righting reflex, visual discrimination response, sensitivity and response to thermal and electrical shock stimuli, and water maze acquisition. The developmental delays of the neonatal animals were transient, with responses becoming comparable to untreated animals later in life. The clinical relevance of these animal data is uncertain.

8.2 Lactation

Risk Summary

Lidocaine is excreted into human milk. When lidocaine was used as an epidural anesthetic for cesarean section in 27 women, a milk:plasma ratio of 1.07 was observed using AUC values. Lactating women undergoing a dental procedure had a 0.4 milk:plasma ratio. In another dental procedure study, a single patient was administered 20 mg of lidocaine and the milk:plasma ratio was reported as 1.1 at five to six hours after injection. These data, and the low concentrations of lidocaine in the plasma after topical administration of ZTLIDO in recommended doses, suggest that a small amount of lidocaine would be ingested orally by a suckling infant. However, caution should be exercised when ZTLIDO is administered to a nursing mother, especially when administered with other local anesthetics.

8.4 Pediatric Use

Safety and effectiveness in pediatric patients have not been established.

8.5 Geriatric Use

Clinical studies of ZTLIDO did not include sufficient numbers of subjects aged 65 and over to determine whether they respond differently from younger subjects. Other reported clinical experience has not identified differences in responses between the elderly and younger patients. In general, dose selection for an elderly patient should be done with caution, usually starting at the low end of the dosing range (e.g., a single topical system), reflecting the greater frequency of decreased hepatic, renal, or cardiac function, and of concomitant disease or other drug therapy.

10 OVERDOSAGE

Lidocaine overdose from cutaneous absorption is rare, but could occur. If there is any suspicion of lidocaine overdose, check drug blood concentration. The management of overdose includes close monitoring, supportive care, and symptomatic treatment. Dialysis is of negligible value in the treatment of acute overdose with lidocaine.

In the absence of massive topical overdose or oral ingestion, evaluation of symptoms of toxicity should include consideration of other etiologies for the clinical effects, or overdosage from other sources of lidocaine or other local anesthetics.

11 DESCRIPTION

ZTLIDO (lidocaine topical system) 1.8% is a single-layer, drug-in-adhesive topical delivery system comprised of an adhesive material containing 36 mg lidocaine, which is applied to a pliable nonwoven cloth backing and covered with a polyethylene terephthalate film release liner. The release liner is removed prior to application to the skin. The size of ZTLIDO is 10 cm × 14 cm × 0.08 cm.

Lidocaine, an amide local anesthetic, is chemically designated as acetamide, 2-(diethylamino)- N-(2,6-dimethylphenyl), has an octanol:water partition ratio of 43 at pH 7.4, and has the following structure:

Each ZTLIDO contains 36 mg of lidocaine (18 mg per gram adhesive) in a non-aqueous base and also contains the following inactive ingredients: butylated hydroxytoluene, dipropylene glycol, isostearic acid, mineral oil, polyisobutylene, silicone dioxide, styrene/isoprene/styrene block copolymer, and terpene resin.

12 CLINICAL PHARMACOLOGY

12.1 Mechanism of Action

Lidocaine is an amide local anesthetic. Lidocaine blocks sodium ion channels required for the initiation and conduction of neuronal impulses.

12.2 Pharmacodynamics

The penetration of lidocaine into intact skin after application of ZTLIDO is sufficient to produce an analgesic effect, but less than the amount necessary to produce a complete sensory block.

12.3 Pharmacokinetics

ZTLIDO has different bioavailability compared to Lidoderm. In a single-dose, crossover study conducted in 53 healthy volunteers, ZTLIDO (lidocaine topical system) 1.8% demonstrated equivalent exposure (AUC) and peak concentration (Cmax) of lidocaine to Lidoderm (lidocaine patch 5%).

Absorption

The amount of lidocaine systemically absorbed from ZTLIDO is directly related to both the duration of application and the surface area over which it is applied. In a pharmacokinetic study, three ZTLIDO topical systems were applied over an area of 420 cm^2of intact skin on the backs of normal healthy volunteers for 12 hours. Blood samples were drawn for determination of lidocaine concentration during the topical system application and for 12 hours after removal of topical systems. The results are summarized in Table 1.

Table 1 Mean ± SD Absorption of lidocaine from ZTLIDO Healthy Volunteers (n = 54, 12-hour application time)
Topical System | Application Site | Area (cm^2) | Cmax(ng/mL) | Tmax(hr) [median (min, max)]
3 Topical systems of ZTLIDO (108 mg) | Back | 420 | 75.1 ± 28.0 | 13.9 (4.0, 18.0)

Repeated application of three Lidoderm patches simultaneously for 12 hours (recommended maximum daily dose), once per day for three days, indicated that the lidocaine concentration does not increase with daily use. The mean plasma pharmacokinetic profile for the 15 healthy volunteers is shown in Figure 1.

Figure 1

Mean lidocaine blood concentrations after three consecutive daily applications of three Lidoderm patches simultaneously for 12 hours per day in healthy volunteers (n = 15).

The pharmacokinetics of ZTLIDO (n = 3 topical systems) was assessed in 12 healthy volunteers with exposure to external heat source (heating pad at medium setting applied for 20 minutes at Time 0 and 8.5 hours) or undergoing moderate exercise (cycling for 30 minutes at a heart rate of 108 bpm at Time 0, 2.5, 5.5 and 8.5 hours) and compared to pharmacokinetics of ZTLIDO at rest. Exposure to external heat at 0 and 8.5 hours results in increased peak plasma levels of lidocaine with a mean (SD) of 160.3 ± 100.1 ng/mL versus the peak plasma levels observed at rest with a mean (SD) of 97.6 ± 36.9 ng/mL. For this reason, instruct patients not to apply heating pads directly to ZTLIDO. Concentrations returned to normal within 4 hours after the heat was removed. No clinically relevant differences in systemic absorption were observed under exercise conditions with a mean (SD) peak plasma concentration of 90.5 ± 25.4 ng/mL.

A separate study in 12 healthy volunteers showed that there was no effect on ZTLIDO pharmacokinetics when the topical system is applied to the administration site after external heat exposure (heating pad at medium setting applied for 15 minutes prior to the topical system application) or after engagement in exercise (walking at a moderate pace on a treadmill for approximately 20 minutes beginning approximately 30 minutes prior to the topical system application).

Distribution

When lidocaine is administered intravenously to healthy volunteers, the volume of distribution is 0.7 to 2.7 L/kg (mean 1.5 ± 0.6 SD, n = 15). At concentrations produced by application of ZTLIDO, lidocaine is approximately 70% bound to plasma proteins, primarily alpha-1-acid glycoprotein. At much higher plasma concentrations (1 to 4 µg/mL of free base), the plasma protein binding of lidocaine is concentration dependent. Lidocaine crosses the placental and blood brain barriers, presumably by passive diffusion.

Elimination

Metabolism:

It is not known if lidocaine is metabolized in the skin. Lidocaine is metabolized rapidly by the liver to a number of metabolites, including monoethylglycinexylidide (MEGX) and glycinexylidide (GX), both of which have pharmacologic activity similar to, but less potent than that of lidocaine. A minor metabolite, 2,6-xylidine, has unknown pharmacologic activity. The blood concentration of this metabolite is negligible following application of ZTLIDO. Following intravenous administration, MEGX and GX concentrations in serum range from 11 to 36% and from 5 to 11% of lidocaine concentrations, respectively.

Excretion:

Lidocaine and its metabolites are excreted by the kidneys. Less than 10% of lidocaine is excreted unchanged. The half-life of lidocaine elimination from the plasma following IV administration is 81 to 149 minutes (mean 107 ± 22 SD, n = 15). The systemic clearance is 0.33 to 0.90 L/minute (mean 0.64 ± 0.18 SD, n = 15).

13 NONCLINICAL TOXICOLOGY

13.1 Carcinogenesis, Mutagenesis, Impairment of Fertility

Carcinogenesis

Long-term studies in animals specifically designed to evaluate the carcinogenic potential of lidocaine or ZTLIDO have not been conducted.

A metabolite, 2,6-xylidine, has been found to be carcinogenic in rats. The clinical significance is not known.

Mutagenesis

Lidocaine HCl was not mutagenic in the in vitro bacterial reverse mutagenicity assay (Ames test). Lidocaine HCl was not clastogenic in the in vitro chromosome aberration assay with human lymphocytes or in the in vivo mouse micronucleus test.

Impairment of Fertility

In a published study, female Sprague-Dawley rats were treated subcutaneously with lidocaine via osmotic pumps starting two weeks prior to mating, and reproductive effects were assessed. Rats dosed up to the high dose of 500 mg/kg/day (approximately 45 times the MRDD on a mg/m^2basis) showed no effects on copulatory rate, pregnancy rate, or the numbers of corpora lutea or implantations.

14 CLINICAL STUDIES

Single-dose treatment with lidocaine patch (currently preferred dosage form term for a patch is topical system) was compared to treatment with vehicle patch (without lidocaine), and to no treatment (observation only) in a double-blind, crossover clinical trial with 35 post-herpetic neuralgia patients. Pain intensity and pain relief scores were evaluated periodically for 12 hours. Lidocaine patch performed statistically better than vehicle patch in terms of pain intensity from 4 to 12 hours.

Multiple-dose, two-week treatment with lidocaine patch was compared to vehicle patch (without lidocaine) in a double-blind, crossover clinical trial of withdrawal-type design conducted in 32 patients, who were considered as responders to the open-label use of lidocaine patch prior to the study. The constant type of pain was evaluated but not the pain induced by sensory stimuli (dysesthesia). Statistically significant differences favoring lidocaine patch were observed in terms of time to exit from the trial (14 versus 3.8 days at p-value <0.001), daily average pain relief, and patient's preference of treatment. About half of the patients also took oral medication commonly used in the treatment of post-herpetic neuralgia. The extent of use of concomitant medication was similar in the two treatment groups.

Based on a clinical study in 54 subjects with ZTLIDO, 47 subjects (87%) had adhesion scores of 0 (≥ 90% adhered) for all evaluations performed every 3 hours during the 12 hours of administration, 7 subjects (13%) had adhesion scores of 1 (≥ 75% to < 90% adhered) for at least one evaluation, and no subjects had scores of 2 or greater (< 75% adhered).

16 HOW SUPPLIED/STORAGE AND HANDLING

ZTLIDO (lidocaine topical system) 1.8% is available as the following:

Carton of 30 topical systems, packaged into individual child-resistant envelopes.

NDC 69557-111-30

STORAGE AND HANDLING

Store at 20° to 25°C (68° to 77°F); excursions permitted between 15° to 30°C (59° to 86°F) [see USP Controlled Room Temperature].

Wash hands thoroughly immediately after handling the topical system. Upon removal, fold the topical system in half so that the adhesive side sticks to itself. Discard used ZTLIDO and pieces of cut ZTLIDO in a manner that prevents accidental contact or ingestion by children, pets or others [see Dosage and Administration (2.2), Warnings and Precautions (5.1)] .

17 PATIENT COUNSELING INFORMATION

Advise the patient to read the FDA-approved patient labeling (Patient Information and Instructions for Use).

Accidental Exposure and Disposal

Advise patients to store ZTLIDO out of the reach of children, pets, and others. Advise patients to dispose of used ZTLIDO by folding used ZTLIDO so that the adhesive side sticks to itself and safely discarding used ZTLIDO or pieces of cut ZTLIDO where children, pets, and others cannot come in contact with them [see Warnings and Precautions (5.1)] .

Proper Application

Advise patients:

- not to apply more than the prescribed number (up to 3 ZTLIDO) [see Dosage and Administration (2.2), Warnings and Precautions (5.2)].
- not to wear ZTLIDO longer than the recommended wearing time (12 hours of every 24 hours) [see Dosage and Administration (2.2), Warnings and Precautions (5.2)].
- to apply ZTLIDO to intact skin [see Warnings and Precautions (5.2)].
- to reattach by pressing firmly on the edges of ZTLIDO that are lifting. If a ZTLIDO topical system comes off completely and will not stick to patient's skin, it should be removed and properly disposed of and a new ZTLIDO topical system should be applied for a total duration of 12 hours of used and new topical system together [see Dosage and Administration (2.1, 2.2)] .

Methemoglobinemia

Inform patients that use of local anesthetics may cause methemoglobinemia, a serious condition that must be treated promptly. Advise patients or caregivers to stop use and seek immediate medical attention if they or someone in their care experience the following signs or symptoms: pale, gray, or blue colored skin (cyanosis); headache; rapid heart rate; shortness of breath; lightheadedness; or fatigue [see Warnings and Precautions (5.3)].

Application Site Reactions

Inform patients that skin irritation and other skin reactions may occur at the site of ZTLido application. If skin reactions occur during wear, instruct patients to remove ZTLido and not to reapply until the skin reaction subsides [see Warnings and Precautions (5.4)]

Eye Exposure

Advise patients to wash hands immediately after handling ZTLIDO and to avoid contact with eyes. Instruct patients to, if eye contact should occur, immediately wash out the eye with water or saline and protect the eye until sensation returns [see Dosage and Administration (2.1), Warnings and Precautions (5.6)] .

Manufactured for:
Scilex Pharmaceuticals Inc.
Palo Alto, CA 94303
USA

ZTLIDO®is a trademark owned by Scilex Pharmaceuticals Inc.

Patented. See: www.scilexpharma.com/patents

© 2021 Scilex Pharmaceuticals Inc. All rights reserved.

SCILEX®
PHARMACEUTICALS

SCILEX®and ZTLIDO®are registered trademarks of Scilex Pharmaceuticals Inc.

PATIENT INFORMATION
ZTLIDO®(ZEE-TEE-LIE-DOH)
(lidocaine topical system)

What is ZTLIDO?

ZTLIDO is a prescription medicine used for relief of pain from damaged nerves (neuropathic pain) that follows healing of shingles. It is not known if ZTLIDO is safe and effective in children.

Do not use ZTLIDO if you:

- have a history of allergic reactions to numbing medicines (anesthetics). Ask your healthcare provider if you are not sure.
- are allergic to any of the ingredients in ZTLIDO. See the end of this leaflet for a complete list of ingredients in ZTLIDO.

Before using ZTLIDO, tell your healthcare provider about all your medical conditions, including if you:

- have liver problems
- have heart or lung problems
- are allergic to para-aminobenzoic acid (PABA) medicines such as procaine, tetracaine, or benzocaine
- have been told that you have glucose-6-phosphate dehydrogenase deficiency
- were born with (congenital) methemoglobinemia or have had methemoglobinemia from an unknown cause
- are pregnant or plan to become pregnant. It is not known if ZTLIDO will harm your unborn baby.
- are breastfeeding or plan to breastfeed. ZTLIDO can pass into your breast milk. Talk to your healthcare provider about the best way to feed your baby if you use ZTLIDO.

Tell your healthcare provider about all the medicines you take,including prescription and over-the-counter medicines, vitamins, and herbal supplements. Especially, tell your healthcare provider if you are using other lidocaine containing products or anesthetic medicines.

How should I use ZTLIDO?

Read the Instructions for Use at the end of this Patient Information leaflet for information about how to apply the ZTLIDO topical system.

- Use ZTLIDO exactly as your healthcare provider tells you to use it.
- Do not apply more than your prescribed number of ZTLIDO. You may apply up to 3 ZTLIDO topical systems at one time.
- A ZTLIDO may be worn only 1 time for up to 12 hours within a 24-hour period (12 hours on and 12 hours off).
- Apply ZTLIDO to intact skin only. Do not apply ZTLIDO to skin that is not intact, such as skin that is cut, scraped, burned, or irritated.
- ZTLIDO topical systems that come off completely or are lifting at the edges may be reattached by firmly pressing down on the topical system or on the lifted areas.
  - If ZTLIDO lifts off the skin or detaches more than 1 time, do nottry to reattach it. Throw it away as described below.
  - If the ZTLIDO you are wearing comes off completely, and will not stick to your skin, throw it away as described below.
  In either of these cases, you may apply a replacement (a new) ZTLIDO topical system. Take off the replacement ZTLIDO at your usual removal time. The total timeyou may wear the used and replacement ZTLIDO is 12 hours.
- You may wear clothing over the ZTLIDO application site.
- Do notapply external heat sources, such as heating pads or electric blankets, directly on ZTLIDO. This may cause increased levels of lidocaine in your blood. You may apply ZTLIDO to a treatment site after moderate heat exposure, such as after 15 minutes of heating pad use on a medium setting.
- ZTLIDO may be used during moderate exercise, such as biking for 30 minutes.
- ZTLIDO may be worn in water such as showering for 10 minutes or bathing for 15 minutes.
- After ZTLIDO is exposed to water, pat the topical system dry. Do notrub the topical system.
- After using ZTLIDO, fold the used ZTLIDO so that the sticky sides stick together. Safely throw away used ZTLIDO and any pieces of cut ZTLIDO where children and pets cannot get to them.
- Wash your hands right away after handling ZTLIDO (after you apply ZTLIDO, when you try to re-attach it, or when you remove it.)
- If you start feeling irritation or burning when applying ZTLIDO, remove the ZTLIDO. Do notreapply ZTLIDO until the irritation or burning goes away.
- If you apply more than 3 ZTLIDO topical systems or apply ZTLIDO for longer than 12 hours of a 24-hour period, call your healthcare provider.

What should I avoid while using ZTLIDO?

- Avoid contact of your hands and fingers with your eyes while handling ZTLIDO. See " Contact of ZTLIDO with your eyes" below.

What are the possible side effects of ZTLIDO?

ZTLIDO may cause serious side effects, including:

- Lidocaine overdosecan happen if you apply more than the prescribed number of ZTLIDO, applying ZTLIDO for longer than 12 hours, have liver problems, use ZTLIDO on skin that is not intact, or if you apply external heat sources directly on ZTLIDO. This can result in increased levels of lidocaine in your blood.
  - Do not apply more than the prescribed number of ZTLIDO.
  - Do not wear ZTLIDO longer than 12 hours.
  - Do not apply ZTLIDO on skin that is not intact, such as skin that is cut, scraped, burned, or irritated.
  - Do not apply external heat sources directly to ZTLIDO. See " How should I use ZTLIDO?" for more information about how to properly use external heat sources when using ZTLIDO.
- A serious blood problem called methemoglobinemia.Methemoglobinemia is a serious blood problem where to much methemoglobin is produced in the blood. Methemoglobinemia can happen with the use of local anesthetics and may not let enough oxygen reach the organs and tissues in your body. Anyone who uses or receives local anesthetics is at risk for methemoglobinemia, but certain people are more likely to have serious medical problems and need to be closely monitored by their healthcare provider during treatment with ZTLIDO, including:
  - people with glucose-6-phosphate dehydrogenase deficiency
  - people with heart of lung problems
  - babies under 6 months of age
  - people who were born with (congenital) or who have had methemoglobinemia from an unknown cause
  - people exposed to certain chemicals at the same time that they use or receive a local anesthetic
  Signs of methemoglobinemia can happen right away or they may not happen for some hours after your have used or received a local anesthetic. It is important to get medical treatment right away to help prevent more serious side effects including seizures, coma, abnormal heart rhythms, and death.
  You or your caregiver should stop using ZTLIDO and get medical help right away if you develop any of the following signs or symptoms:

- pale, gray, or blue colored skin
- headache

- rapid heart beat
- shortness of breath

- lightheadedness
- tiredness

- Application site reactions.Skin irritation and other skin reactions at the ZTLIDO application site are common and are usually mild. These reactions can happen during or right after treatment with ZTLIDO. Application site reactions will usually go away within a few minutes to hours. Symptoms of application site reactions may include:

- blisters
- bruising
- burning or abnormal sensation
- change or loss of color of your skin
- swelling, redness, and pain of the skin

- peeling or flaking of skin
- irritation
- pimple-like raised skin
- itching

If you develop a skin reaction while wearing ZTLIDO, remove it. Do notreapply ZTLIDO until the site reaction goes away.

- Allergic reactionscan happen if you have a history of allergic reactions to numbing medicines (anesthetics). Tell your healthcare provider right away if you have any symptoms of an allergic reaction such as swelling or shortness of breath.
- Contact of ZTLIDO with your eyescan happen if you touch your eyes while handling the topical system and can cause severe eye irritation. Avoid eye contact with your hands and fingers while handling ZTLIDO. Wash your hands right away after handling ZTLIDO. If the medicine in ZTLIDO comes in contact with your eye, wash out your eye with water or saline right away. Protect the eye (for example eye glasses or eye wear) until the numbness goes away.

These are not all the possible side effects of ZTLIDO.

Call your doctor for medical advice about side effects. You may report side effects to FDA at 1-800-FDA-1088.

How should I store ZTLIDO?

- Store ZTLIDO at room temperature between 68°F to 77°F (20°C to 25°C).
- Keep ZTLIDO topical system in the original packaging unit until ready for use.
- Each ZTLIDO topical system comes in a child-resistant envelope.

Keep ZTLIDO and all medicines out of the reach of children, pets, and others.

General information about the safe and effective use of ZTLIDO.

Medicines are sometimes prescribed for purposes other than those listed in a Patient Information leaflet. Do not use ZTLIDO for a condition for which it was not prescribed. Do not give ZTLIDO to other people, even if they have the same symptoms you have. It may harm them. You can ask your pharmacist or healthcare provider for information about ZTLIDO that is written for health professionals.

What are the ingredients in ZTLIDO?

Active ingredient:lidocaine

Inactive ingredients:butylated hydroxytoluene, dipropylene glycol, isostearic acid, mineral oil, polyisobutylene, silicone dioxide, styrene/isoprene/styrene block copolymer, and terpene resin.

Manufactured for:Scilex Pharmaceuticals Inc., Palo Alto, CA 94303

ZTLIDO®is a trademark owned by Scilex Pharmaceuticals Inc. © 2021 Scilex Pharmaceuticals Inc. All rights reserved.

SCILEX®
PHARMACEUTICALS

For more information call [1-844-SCILEX1] or visit www.ZTLIDO.com.

This Patient Information has been approved by the U.S. Food and Drug Administration.

Issued: 4/2021

Instructions for Use
ZTLIDO®(ZEE-TEE-LIE-DOH)
(lidocaine topical system)

Read this Instructions for Use before you start using ZTLIDO and each time you get a refill. There may be new information. This information does not take the place of talking to your healthcare provider about your medical treatment or condition.

Important information:

- One ZTLIDO (lidocaine topical system) 1.8% provides equivalent lidocaine exposure to one Lidoderm® (lidocaine patch 5%).
- ZTLIDO is for use on intact skin only.
- ZTLIDO comes in a child-resistant envelope. Do not open the ZTLIDO envelope until you are ready to use it.
- Apply the prescribed number of ZTLIDO topical systems at one time. Clothing may be worn over ZTLIDO.
- You should only use a maximum of 3 ZTLIDO topical systems at a time.
- Keep your prescribed number of ZTLIDO topical systems on for up to 12 hours within a 24-hour period (12 hours on and 12 hours off).
- ZTLIDO may be used during moderate exercise, such as biking for 30 minutes.
- ZTLIDO may be worn in water such as showering for 10 minutes or bathing for 15 minutes.
- After ZTLIDO is exposed to water, pat the topical system dry. Do not rub the topical system.
- ZTLIDO topical systems that have come off completely or are lifting at the edges may be re-attached to the affected area by firmly pressing down on the topical system or on the lifted areas.
  - If ZTLIDO lifts off the skin or detaches more than 1 time, do nottry to re-attach it. Throw it away (See Step 6).
  - If the ZTLIDO you are wearing comes off completely, and will not stick to your skin, throw it away (see Step 6).
  In either of these cases, you may put on a replacement (a new) ZTLIDO topical system. Take off the replacement ZTLIDO at your usual removal time. The total time that you may wear the used and replacement ZTLIDO is 12 hours.

Wash your hands well right away after handling ZTLIDO (when you apply ZTLIDO, when you re-attach it, or when you remove it). Avoid eye contact with your hands and fingers while handling ZTLIDO.

Figure A: ZTLIDO Topical System

Applying your ZTLIDO topical system:

Step 1:Select the application site.

- ZTLIDO should only be applied to clean, dry, and intact skin to cover the most painful area.

Step 2:Using scissors, carefully cut the envelope along the dotted line and open it to remove ZTLIDO.

- Do not use ZTLIDO if it is damaged. Throw it away and get a new one.
- ZTLIDO may be cut into smaller sizes with scissors prior to removal of the transparent release liner.

Step 3a:Remove the transparent release liner before applying ZTLIDO to the skin. Apply ZTLIDO right away after removing the transparent release liner. Apply ZTLIDO only to intact skin.

Step 3b:Place the adhesive side of ZTLIDO to skin, while not touching the sticky side. Smooth the ZTLIDO using your hands and firmly press to make sure it sticks well to skin.

Step 4:Wash your hands well right away after applying ZTLIDO.

- Avoid contact of your hands or fingers with your eyes until after you wash your hands.

Removing your ZTLIDO topical system:

Step 5:Remove ZTLIDO from your skin after you have worn it for up to 12 hours.

- Fold the used ZTLIDO so that the sticky sides stick together.

Step 6:Throw away the used whole or cut pieces of ZTLIDO where children and pets cannot get to them.

- Wash your hands well right away after removing ZTLIDO. Avoid contact of your hands and fingers with your eyes until after you wash your hands.

How to reattach ZTLIDO or apply a replacement ZTLIDO:

- If the ZTLIDO you are wearing comes off completely or lifts at the edges, reattach to the affected area by pressing firmly on the edges of the topical system or lifted areas. If ZTLIDO lifts off the skin or comes off completely more than 1 time, do nottry to re-attach it. Throw away the used ZTLIDO as instructed above in Step 6.
- If the ZTLIDO you are wearing comes off completely and will not stick to your skin, throw away the used ZTLIDO as instructed above in Step 6.
- Pat dry the area of skin if ZTLIDO came off while swimming or showering.
- Apply a replacement ZTLIDO the same way you would apply a new ZTLIDO as described above in Steps 1 through 6.
- Remove the replacement ZTLIDO at your usual removal time as described above in Steps 5 and 6.
- The total timeyou may wear the used and replacement ZTLIDO is 12 hours.

Manufactured for:
Scilex Pharmaceuticals Inc.
Palo Alto, CA 94303
USA

ZTLIDO®is a trademark owned by Scilex Pharmaceuticals Inc.
© 2021 Scilex Pharmaceuticals Inc. All rights reserved.

SCILEX®
PHARMACEUTICALS

Revised: 4/2021

PACKAGE LABEL

PRINCIPAL DISPLAY PANEL - lidocaine patch 1.8% CARTON LABEL

NDC 69557-111-30

ZTlido™

(lidocaine topical system) 1.8%*

For topical use only.

*One ZTlido™ (lidocaine topical system) 1.8%provides equivalent lidocaine exposure to one Lidoderm® (lidocaine patch 5%).

Inactive ingredients: butylated hydroxytoluene, dipropylene glycol, isostearic acid, mineral oil, polyisobutylene, silicone dioxide, styrene/isoprene/styrene block copolymer, and terpene resin.

DOSAGE:For dosage and full prescribing information, please read accompanying product information.

Store at 68-77°F (20-25°C). [See USP Controlled Room Temperature].

WARNING:Store and dispose of ZTlido™ out of the reach of children, pets, and others.

30 TOPICAL SYSTEMS

30 Envelopes Containing 1 Topical System Each

SCILEX ™ Rx Only

PHARMACEUTICALS

Manufactured by: Oishi Koseido Co., Ltd., Tosu, Saga, Japan
Manufactured for: SCILEX Pharmaceuticals Inc., San Diego, CA 92121
Active Ingredient Made in Spain